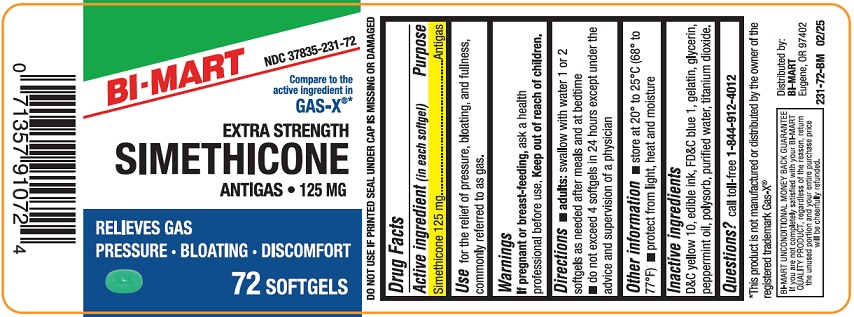 DRUG LABEL: Extra Strength Simethicone
NDC: 37835-231 | Form: CAPSULE, LIQUID FILLED
Manufacturer: Bi-Mart
Category: otc | Type: HUMAN OTC DRUG LABEL
Date: 20250401

ACTIVE INGREDIENTS: DIMETHICONE 125 mg/1 1
INACTIVE INGREDIENTS: PEPPERMINT OIL; GELATIN; WATER; POLYSORBATE 20; GLYCERIN; FD&C BLUE NO. 1; TITANIUM DIOXIDE; D&C YELLOW NO. 10

Active Ingredient (in each softgel)

Simethicone 125 mg

Purpose

Antigas

Use

for the relief of pressure, bloating, and fullness, commonly referred to as gas.

Warnings

If pregnant or breast-feeding,ask a health professional before use.

Keep out of reach of children.

Directions

- adults:swallow with water 1 or 2 softgels as needed after meals and at bedtime
- do not exceed 4 softgels in 24 hours except under the advice and supervision of a physician

Other Information

- store at 20° to 25°C (68° to 776°F)
- protect from light, heat, and moisture

Inactive Ingredients

D&C Yellow 10, edible ink, FD&C blue 1, gelatin, glycerin, peppermint oil, polysorb, purified water, titanium dioxide.

Questions?

Call toll-free 1-844-912-4012